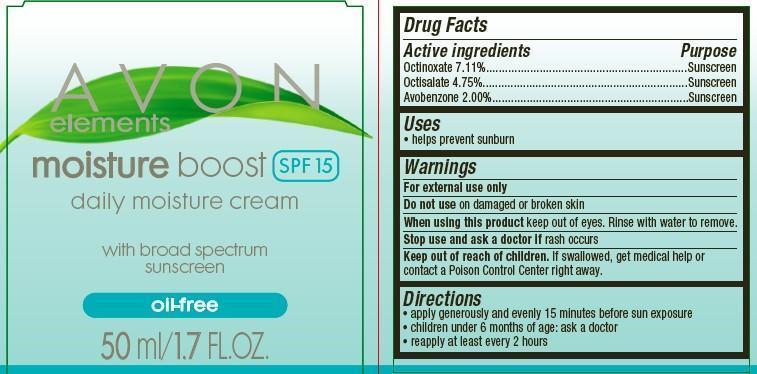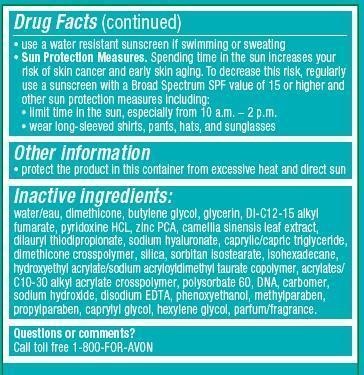 DRUG LABEL: Avon Elements
NDC: 10096-0300 | Form: CREAM
Manufacturer: New Avon LLC
Category: otc | Type: HUMAN OTC DRUG LABEL
Date: 20160219

ACTIVE INGREDIENTS: OCTINOXATE 71.1 mg/1 mL; OCTISALATE 47.5 mg/1 mL; AVOBENZONE 20 mg/1 mL

Active Ingredients
Octinoxate 7.11%....................................
Octisalate 4.75%.....................................
Avobenzone 2.00%.................................

Purpose
............... Sunscreen
............... Sunscreen
.............. Sunscreen

Uses

- helps prevent sunburn

Warnings
For external use only

Do not use on damaged or broken skin

When using this product keep out of eyes. Rinse with water to remove.

Stop use and ask a doctor if rash occurs

Keep out of reach of children. If swallowed, get medical help or contact a Poison Control Center right away.

Directions

- apply generously and evenly 15 minutes before sun exposure
- children under 6 month of age:ask a doctor
- reapply at least every 2 hours
- use a water resistant sunscreen if swimming or sweating
- Sun Protection Measures. Spending time in the sun increases your risk of skin cancer and early skin aging. To decrease this risk, regularly
  use a sunscreen with a Broad Spectrum SPF value of 15 or higher and other sun protection measures including:
  • limit time in the sun, especially from 10 a.m. – 2 p.m.
  • wear long-sleeved shirts, pants, hats, and sunglasses

Other Information

- protect the product in this container from excessive heat and direct sun.

Inactive ingredients:
water/eau, dimethicone, butylene glycol, glycerin, DI-C12-15 alkyl fumarate, pyridoxine HCL, zinc PCA, camellia sinensis leaf extract,dilauryl thiodipropionate, sodium hyaluronate, caprylic/capric triglyceride, dimethicone crosspolymer, silica, sorbitan isostearate, isohexadecane,
hydroxyethyl acrylate/sodium acryloyldimethyl taurate copolymer, acrylates/C10-30 alkyl acrylate crosspolymer, polysorbate 60, DNA, carbomer, sodium hydroxide, disodium EDTA, phenoxyethanol, methylparaben, propylparaben, caprylyl glycol, hexylene glycol, parfum/fragrance.

Questions or comments?
Call toll free 1-800-FOR-AVON